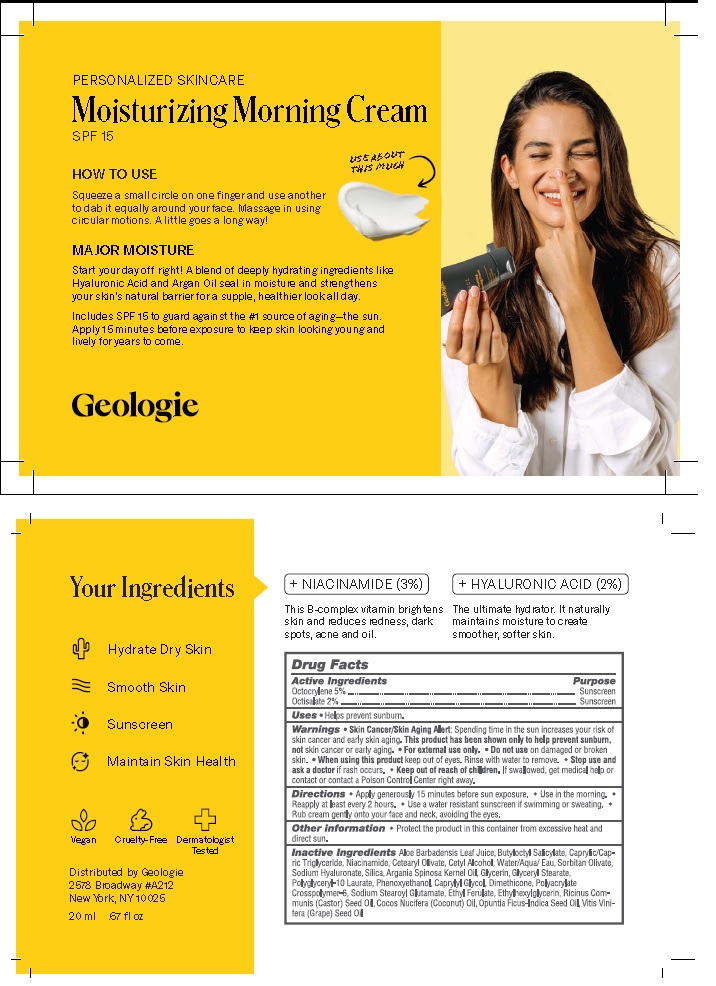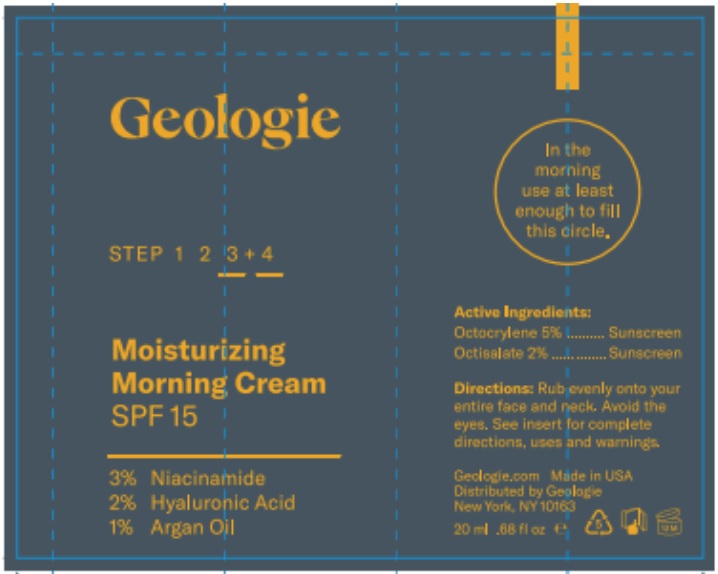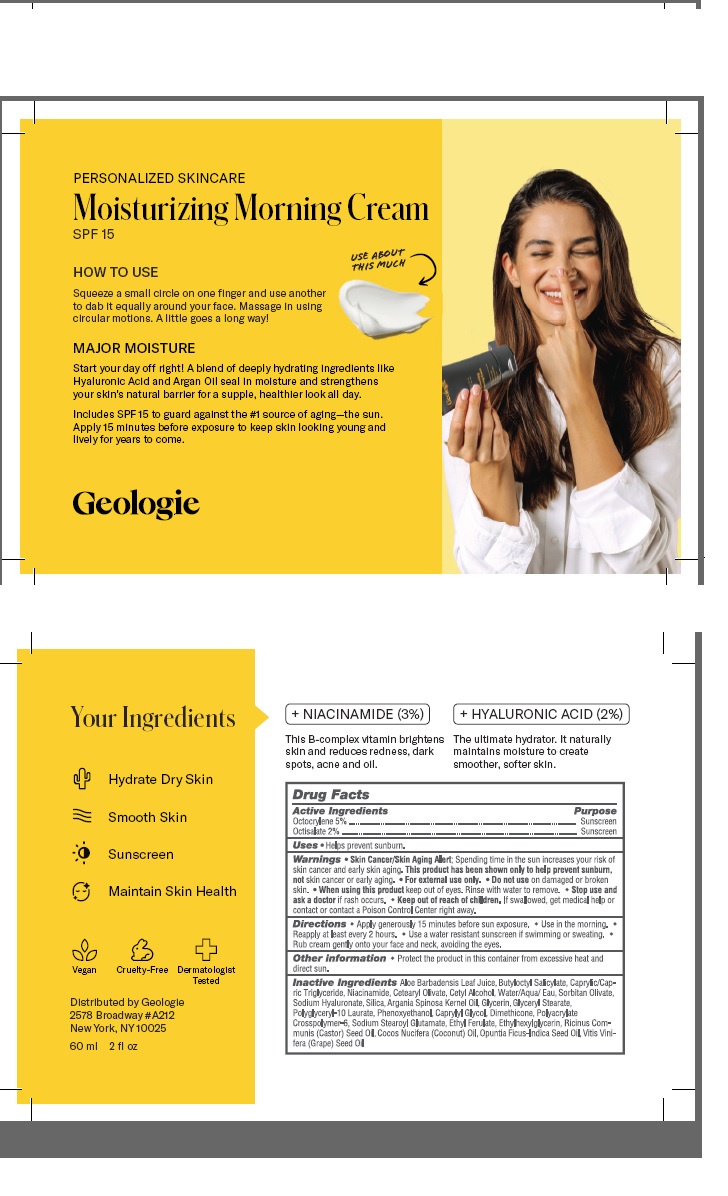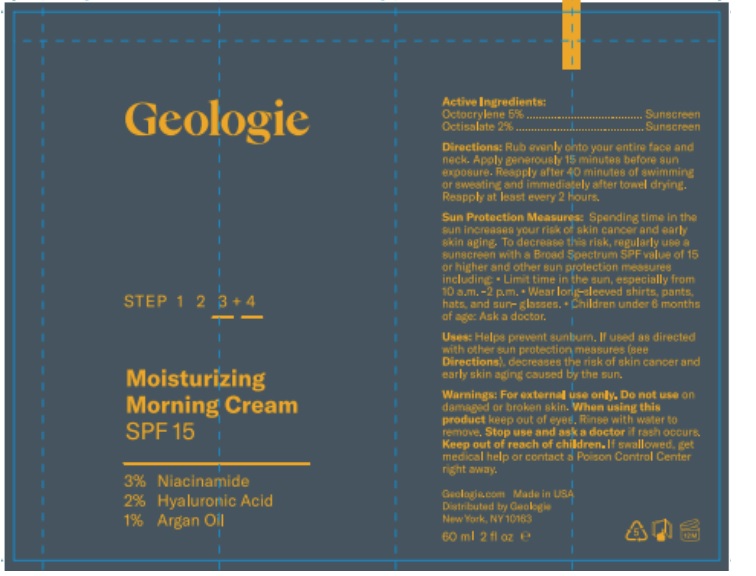 DRUG LABEL: Moisturizing Morning Cream SPF 15
NDC: 54111-172 | Form: CREAM
Manufacturer: Bentley Laboratories, LLC
Category: otc | Type: HUMAN OTC DRUG LABEL
Date: 20241211

ACTIVE INGREDIENTS: OCTOCRYLENE 5.0 g/100 mL; OCTISALATE 2.0 g/100 mL
INACTIVE INGREDIENTS: ALOE VERA LEAF; BUTYLOCTYL SALICYLATE; MEDIUM-CHAIN TRIGLYCERIDES; NIACINAMIDE; CETEARYL OLIVATE; CETYL ALCOHOL; WATER; SORBITAN OLIVATE; HYALURONATE SODIUM; SILICON DIOXIDE; ARGAN OIL; GLYCERIN; GLYCERYL MONOSTEARATE; POLYGLYCERYL-10 LAURATE; PHENOXYETHANOL; CAPRYLYL GLYCOL; DIMETHICONE; AMMONIUM ACRYLOYLDIMETHYLTAURATE, DIMETHYLACRYLAMIDE, LAURYL METHACRYLATE AND LAURETH-4 METHACRYLATE COPOLYMER, TRIMETHYLOLPROPANE TRIACRYLATE CROSSLINKED (45000 MPA.S); SODIUM STEAROYL GLUTAMATE; ETHYL FERULATE; ETHYLHEXYLGLYCERIN; CASTOR OIL; COCONUT OIL; OPUNTIA FICUS-INDICA SEED OIL; GRAPE SEED OIL

Moisturizing Morning Cream SPF 15

DRUG FACTS

Active Ingredients

Octocrylene 5%

Octisalate 2%

Purpose .... Sunscreem

INDICATIONS AND USAGE

Uses: Helps prevent sunburn.

WARNINGS

Warnings •Skin Cancer/Skin Aging Alert: Spending too much time in the sun increases your risk of
skin cancer and early skin aging. This product has been shown to only help prevent sunburn,
not skin cancer or early skin aging. • For external use only. • Do not use on damaged or broken
skin. • When using this product, keep out of eyes. Rinse with water to remove. • Stop use and
ask a doctor if rash occurs.

KEEP OUT OF REACH OF CHILDREN

Keep out of the reach of children. If swallowed get medical help or contact a Poison Control center right away.

DOSAGE AND ADMINISTRATION

Directions• Apply generously 15 minutes before sun exposure. • Use in the morning.
• Reapply every 2 hours. • Use a water resistant sunscreen if swimming or sweating. • Rub
cream gently into your face and neck, avoiding the eyes.

Other information • Protect the product in this container from excessive heat and direct sun.

INACTIVE INGREDIENT

Inactive Ingredients Aloe Barbadensis Leaf Juice, Butyloctyl Salicylate, Caprylic/Cap-
ric Triglyceride, Niacinamide, Cetearyl Olivate, Cetyl Alcohol, Water (Aqua/Eau), Sorbitan Olivate,
Sodium Hyaluronate, Silica, Argania Spinosa Kernel Oil, Glycerin, Glyceryl Stearate,
Polyglyceryl-10 Laurate, Phenoxyethanol, Caprylyl Glycol, Dimethicone, Polyacrylate
Crosspolymer-6, Sodium Stearoyl Glutamate, Ethyl Ferulate, Ethylhexylglycerin, Ricinus Com-
munis (Castor) Seed Oil, Cocos Nucifera (Coconut) Oil, Opuntia Ficus-Indica Seed Oil, Vitis Vini-
fera (Grape) Seed Oil

Product Labeling

Moisturizing Morning Cream
SPF 15

Distributed by Geologie
2578 Broadway #A212
New York, NY 10025

20 ml .67 fl oz

20 mL Label

60 mL Label

res